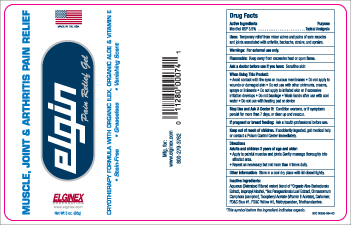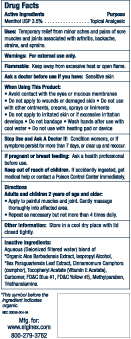 DRUG LABEL: Elgin Pain Relief
NDC: 30056-004 | Form: GEL
Manufacturer: Eco-Logics, Inc.
Category: otc | Type: HUMAN OTC DRUG LABEL
Date: 20251018

ACTIVE INGREDIENTS: MENTHOL 35 mg/1 g
INACTIVE INGREDIENTS: CAMPHOR (NATURAL); METHYLPARABEN; TROLAMINE; FD&C YELLOW NO. 5; ALOE VERA LEAF; ISOPROPYL ALCOHOL; ILEX PARAGUARIENSIS LEAF; ALPHA-TOCOPHEROL; FD&C BLUE NO. 1; CARBOMER HOMOPOLYMER TYPE C (ALLYL PENTAERYTHRITOL CROSSLINKED); WATER

OTC-ACTIVE INGREDIENT SECTION

Active Ingedients Purpose

Menthol USP 3.5%................... Topical Analgesic

PURPOSE

Menthol USP 3.5% Topical Analgesic

Uses

Temporary relief from minor pains of sore muscles and jpintsassociated with arthritis, backache, strains, and sprains..

Warning

For external use only.

Directions

Adults and children 2 years of age and older:

Apply to painful muscles and joint. Genthly massage thoroughly into affected area.

Repeat as necessary but not more than 4 times daily.

Ask a doctor before use if you have Sensitive skin.

When Using this Product:

Avoid contact with the eyes or muscous membranes

Do not apply to wounds or damaged skin

Do not use with other ointmens, creams, sprays, or linaments.

Do not apply to irritated skin or if excessive irration develops

Do not bandage

Wash hands after use with cool water

Do not use with heating pad or device.

Stop Use and Ask Doctor If: Condition worsens, or if symtoms persist for more than 7 days, or clear up and reoccur.

If Pregnant or breast feeding: Ask a health professional before use.

Keep out of reach of children. If accidentally ingested, get medicalhelp or contact a Poisan Control Center immediately.

immedaAqueous (Deionized filtered water) blend of certified * Organic Aloe Barbadensis Extract, Isopropyl Alcohol, *IlexParaguariensis leaf extract, Cinnamomum Camphora (camphor),Tocopheryl Avetate (Vitamin E Acetate), Carbomer, FD&C Blue #1, FD&C Yellow #5, Methylparaben, Triethanolamine.

Directions:

Adults and children 2 years of age and older

Apply to painful muscles and joints. Genthly massage thoroughly into affected area.

Repeat as necessary but not more than 4 times daily.

Other infirmation:

Other Information: Store in a cool dry place with lid closed tightly.

Inactive Ingredients

Aqueous (Deionozed filtered water) blend of certified * Organic Aloe Barbadensis Extract, Isopropyl Alcohol, *Ilex Paraguariensis Leaf Extract, Cinnamomum Camphora (camphor),Tocopheryl Acetate (Vitamin E Acetate), Carbomer, FDC Blue #1, FDCYellow #5, Methylparaben, Triethanolamine.